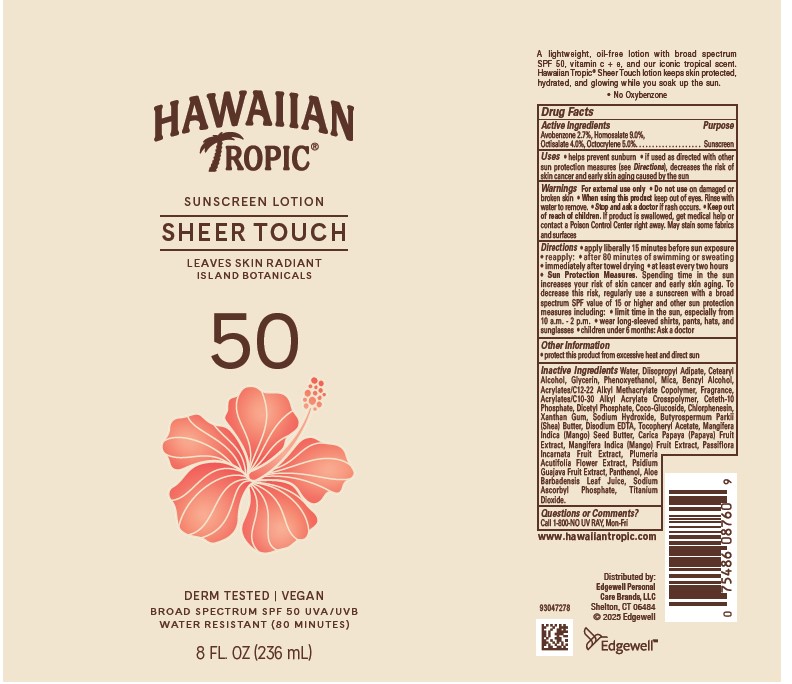 DRUG LABEL: HAWAIIAN TROPIC
NDC: 63354-493 | Form: LOTION
Manufacturer: Edgewell Personal Care Brands LLC
Category: otc | Type: HUMAN OTC DRUG LABEL
Date: 20251231

ACTIVE INGREDIENTS: HOMOSALATE 9 g/100 g; AVOBENZONE 2.7 g/100 g; OCTOCRYLENE 5 g/100 g; OCTISALATE 4 g/100 g
INACTIVE INGREDIENTS: BENZYL ALCOHOL; PAPAYA; MANGO; COCO GLUCOSIDE; ALPHA-TOCOPHEROL ACETATE; MANGIFERA INDICA SEED BUTTER; GUAVA; ALOE VERA LEAF; SODIUM ASCORBYL PHOSPHATE; MICA; CETETH-10 PHOSPHATE; CETOSTEARYL ALCOHOL; PHENOXYETHANOL; TITANIUM DIOXIDE; DIHEXADECYL PHOSPHATE; CHLORPHENESIN; SHEA BUTTER; PLUMERIA RUBRA FLOWER; PANTHENOL; DIISOPROPYL ADIPATE; XANTHAN GUM; PASSIFLORA INCARNATA FRUIT; GLYCERIN; EDETATE DISODIUM; WATER; SODIUM HYDROXIDE

Active Ingredients

Avobenzone 2.7%, Homosalate 9.0%, Octisalate 4.0%, Octocrylene 5.0%.

Purpose

Sunscreen

Uses

• helps prevent sunburn • if used as directed with other sun protection measures (see Directions), decreases the risk of skin cancer and early skin aging caused by the sun

Warnings

For external use only

May stain some fabrics and surfaces

Do not use

on damaged or broken skin

When using this product

keep out of eyes. Rinse with water to remove.

Stop and ask a doctor

if rash occurs.

Keep out of reach of children.

If product is swallowed, get medical help or contact a Poison Control Center right away.

Directions

• apply liberally 15 minutes before sun exposure • reapply: • after 80 minutes of swimming or sweating • immediately after towel drying • at least every two hours • Sun Protection Measures. Spending time in the sun increases your risk of skin cancer and early skin aging. To decrease this risk, regularly use a sunscreen with a broad spectrum SPF value of 15 or higher and other sun protection measures including: • limit time in the sun, especially from 10 a.m. - 2 p.m. • wear long-sleeved shirts, pants, hats, and sunglasses • children under 6 months: Ask a doctor

Inactive Ingredients

Water, Diisopropyl Adipate, Cetearyl Alcohol, Glycerin, Phenoxyethanol, Mica, Benzyl Alcohol, Acrylates/C12-22 Alkyl Methacrylate Copolymer, Fragrance, Acrylates/C10-30 Alkyl Acrylate Crosspolymer, Ceteth-10 Phosphate, Dicetyl Phosphate, Coco-Glucoside, Chlorphenesin, Xanthan Gum, Sodium Hydroxide, Butyrospermum Parkii (Shea) Butter, Disodium EDTA, Tocopheryl Acetate, Mangifera Indica (Mango) Seed Butter, Carica Papaya (Papaya) Fruit Extract, Mangifera Indica (Mango) Fruit Extract, Passiflora Incarnata Fruit Extract, Plumeria Acutifolia Flower Extract, Psidium Guajava Fruit Extract, Panthenol, Aloe Barbadensis Leaf Juice, Sodium Ascorbyl Phosphate, Titanium Dioxide.

Other Information

• protect this product from excessive heat and direct sun

Questions or Comments?

Call 1-800-NO UV RAY, Mon-Fri

Principal Display Panel

HAWAIIAN
TROPIC(R)
SUNSCREEN LOTION
SHEER TOUCH
LEAVES SKIN RADIANT
ISLAND BOTANICALS
50
DERM TESTED | VEGAN
BROAD SPECTRUM SPF 50 UVA/UVB
WATER RESISTANT (80 MINUTES)
8 FL. OZ (236 mL)